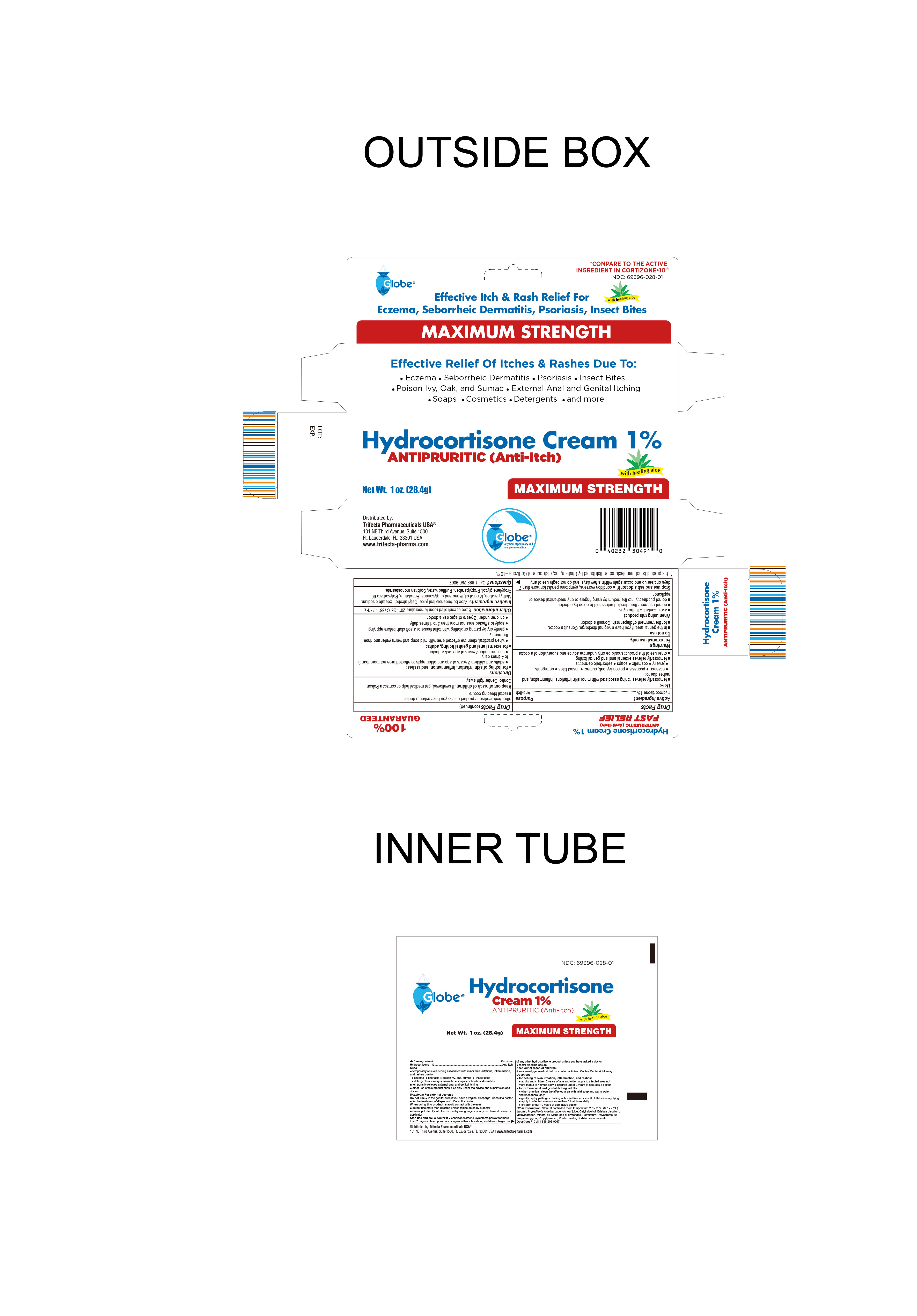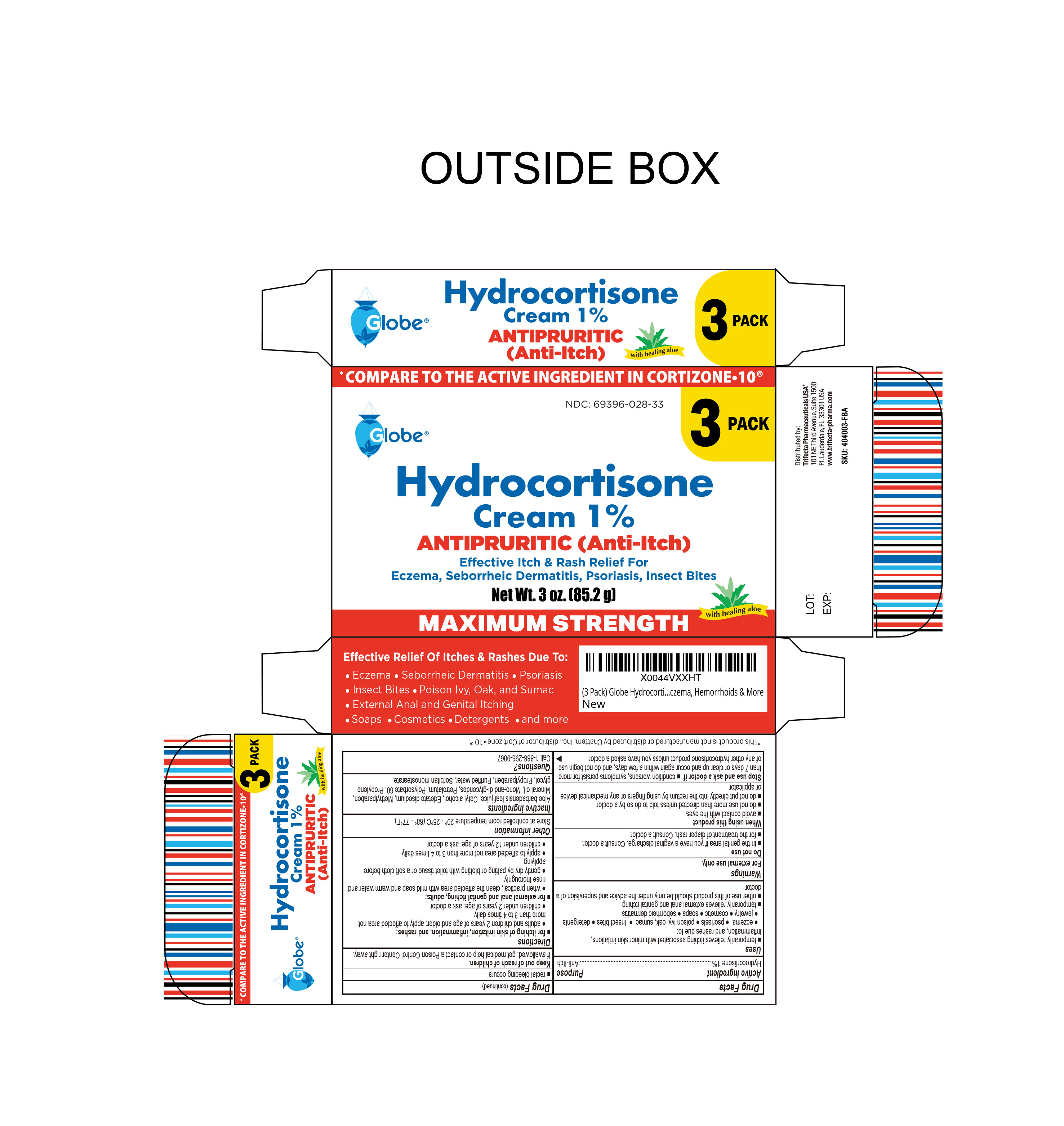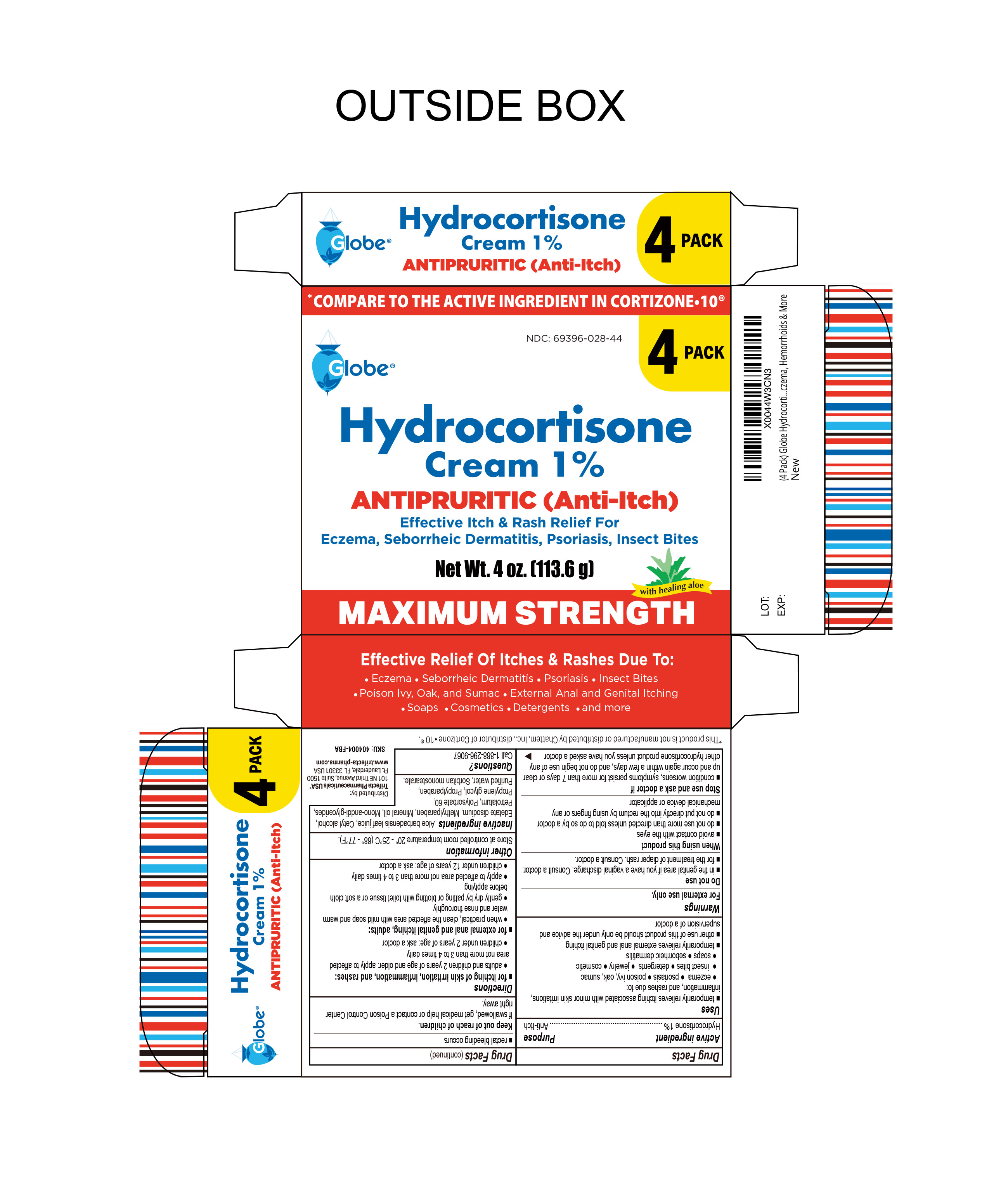 DRUG LABEL: Hydrocortisone Cream
NDC: 69396-028 | Form: CREAM
Manufacturer: Trifecta Pharmaceuticals USA
Category: otc | Type: HUMAN OTC DRUG LABEL
Date: 20250508

ACTIVE INGREDIENTS: HYDROCORTISONE 1 g/100 g
INACTIVE INGREDIENTS: POLYSORBATE 60; EDETATE DISODIUM; WATER; SORBITAN STEARATE; PETROLATUM; ALOE VERA LEAF; CETYL ALCOHOL; GLYCERYL MONO- AND DIPALMITOSTEARATE; METHYLPARABEN; MINERAL OIL; PROPYLENE GLYCOL; PROPYLPARABEN

Hydrocortisone Cream 1%

Active Ingredient

Hydrocortisone 1%

Purpose

Anti-Itch

Uses

Temporarily relieves itching associated with minor skin irritations, inflammation and rashes due to:

- eczema
- seborrheic dermatitis
- psoriasis
- insect bites
- poison ivy, oak, sumac
- soaps
- detergents
- cosmetics
- jewelry
- external genital and anal itching

Other uses of this product should be only under the advice and supervision of a doctor

Keep out of reach of children

If swallowed, get medical help or contact a Poison Control Center immediately.

Warnings

- for external use only
- avoid contact with eyes
- do not put this product into the rectum by using fingers or any mechanical device or applicator

For External Anal Itching Users:

- do not exceed the recommended daily dosage unless directed by a doctor
- in case of bleeding, consult a doctor promptly
- children under 12 years of age: consult a doctor

Before using any medication, read all label directions. Keep this carton as it contains important information

Stop using this product and ask a doctor

- in case of bleeding
- if condition worsens or if symptoms persist for more than 7 days or clear up and occur again within a few days
- before you begin using any other hydrocortisone product

Do not use this product and ask a doctor

- If you have a vaginal discharge
- before treating diaper rash
- before using on children under 2 years of age

Directions

- When practical, cleanse the affected area with mild soap and warm water and rinse thoroughly
- gently dry by patting or blotting with toilet tissue or a soft cloth before applying
- adults and children 12 years of age and older, apply to the affected area not more than 3 to 4 times daily
- children under 12 years of age: do not use, consult a doctor

Inactive Ingredients

Aloe barbadensis leaf juice, ethylparaben, glycerin, glycerol monostearate, hexadecanol, mineral water, octadecannol, petrolatum, purified water, sodium dodecyl sulfate

Other Information

- to open; unscrew cap and pull tab to remove foil seal
- if seal has been broken, do not use this product. Return product to the store where you bought it
- store at controlled room temperature 15°-30°C (59°-86°F)
- see carton or tube crimp for lot number and expiration date

Other Information

Distributed By:

Trifecta Pharmaceuticals USA®

101 NE Third Avenue, Suite 1500

Ft. Lauderdale, FL. 33301 USA

www.trifecta-pharma.com

1-888-296-9067